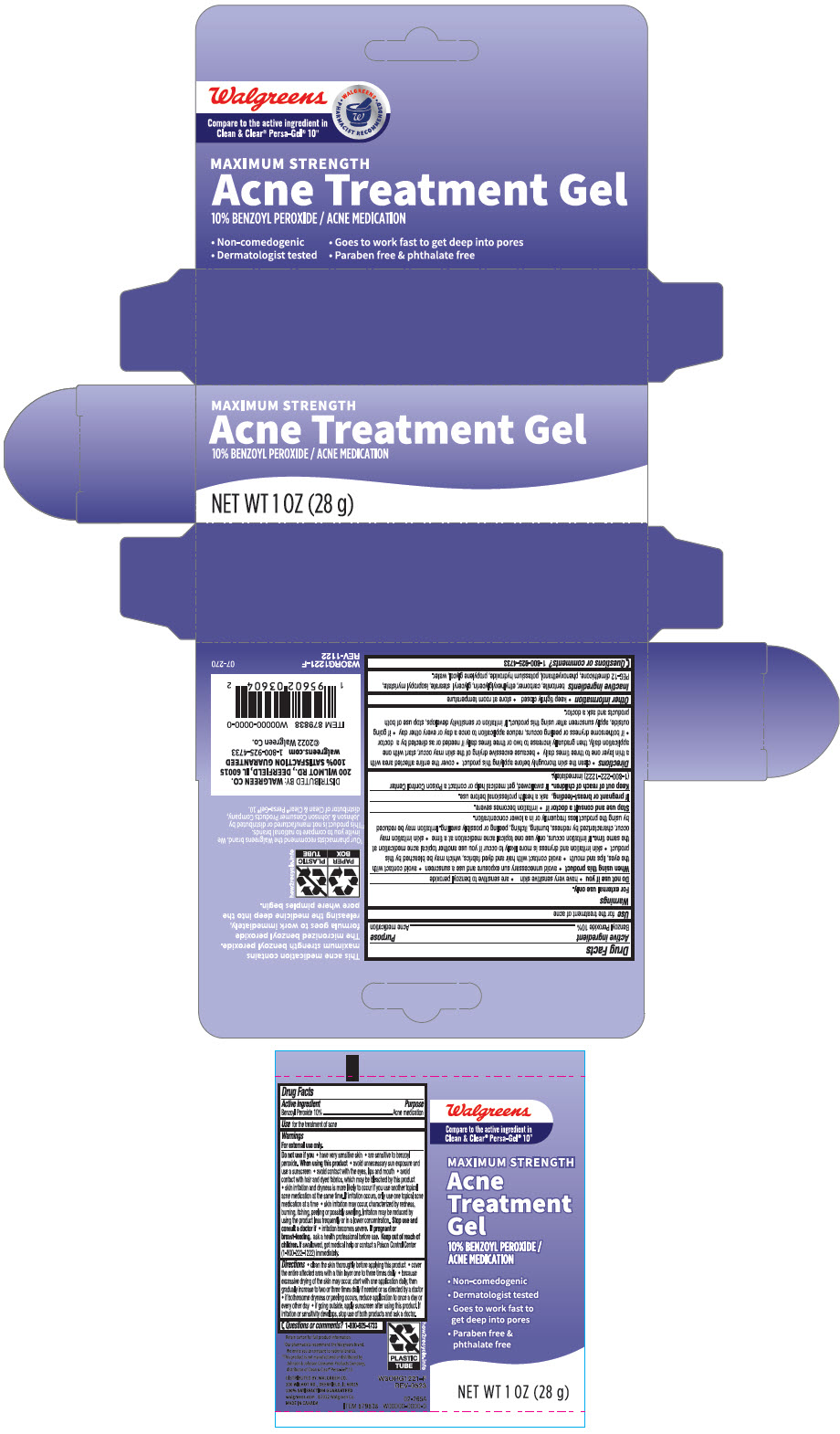 DRUG LABEL: Walgreens Maximum Strength Acne Treatment
NDC: 0363-8798 | Form: GEL
Manufacturer: Walgreen Company
Category: otc | Type: HUMAN OTC DRUG LABEL
Date: 20240603

ACTIVE INGREDIENTS: Benzoyl Peroxide 100 mg/1 g
INACTIVE INGREDIENTS: Bentonite; CARBOMER HOMOPOLYMER, UNSPECIFIED TYPE; Ethylhexylglycerin; GLYCERYL MONOSTEARATE; Isopropyl Myristate; PEG-12 DIMETHICONE (300 CST); Phenoxyethanol; Potassium Hydroxide; Propylene Glycol; Water

Walgreens Maximum Strength Acne Treatment Gel

Drug Facts

Active ingredient

Benzoyl Peroxide 10%

Purpose

Acne medication

Use

for the treatment of acne

Warnings

For external use only.

Do not use if you

- have very sensitive
- are sensitive to benzoyl peroxide

When using this product

- avoid unnecessary sun exposure and use a sunscreen
- avoid contact with the eyes, lips and mouth
- avoid contact with hair and dyed fabrics, which may be bleached by this product
- skin irritation and dryness is more likely to occur if you use another topical acne medication at the same time. If irritation occurs, only use one topical acne medication at a time
- skin irritation may occur, characterized by redness, burning, itching, peeling, or possibly swelling. Irritation may be reduced by using the product less frequently or in a lower concentration.

Stop use and ask a doctor if

- irritation becomes severe.

PREGNANCY OR BREAST FEEDING

If pregnant or breast-feeding, ask a health professional before use.

Keep out of reach of children. If swallowed, get medical help or contact a Poison Control Center (1-800-222-1222) immediately.

Directions

- clean the skin thoroughly before applying this product
- cover the entire affected area with a thin layer one to three times daily
- because excessive drying of the skin may occur, start with one application daily, then gradually increase to two to three times daily if needed or as directed by a doctor
- if bothersome dryness or peeling occurs, reduce application to once a day or every other day
- if going outside, apply sunscreen after using this product. If irritation or sensitivity develops, stop use of both products and ask a doctor.

Other information

- keep tightly closed
- store at room temperature

Inactive ingredients

bentonite, carbomer, ethylhexylglycerin, glyceryl stearate, isopropyl myristate, PEG-12 dimethicone, phenoxyethanol, potassium hydroxide, propylene glycol, water.

Questions or comments?

1-800-925-4733

DISTRIBUTED BY: WALGREEN CO.
200 WILMOT RD., DEERFIELD, IL 60015

PRINCIPAL DISPLAY PANEL - 28 g Tube Carton

MAXIMUM STRENGTH
Acne Treatment Gel
10% BENZOYL PEROXIDE / ACNE MEDICATION

NET WT 1 OZ (28 g)